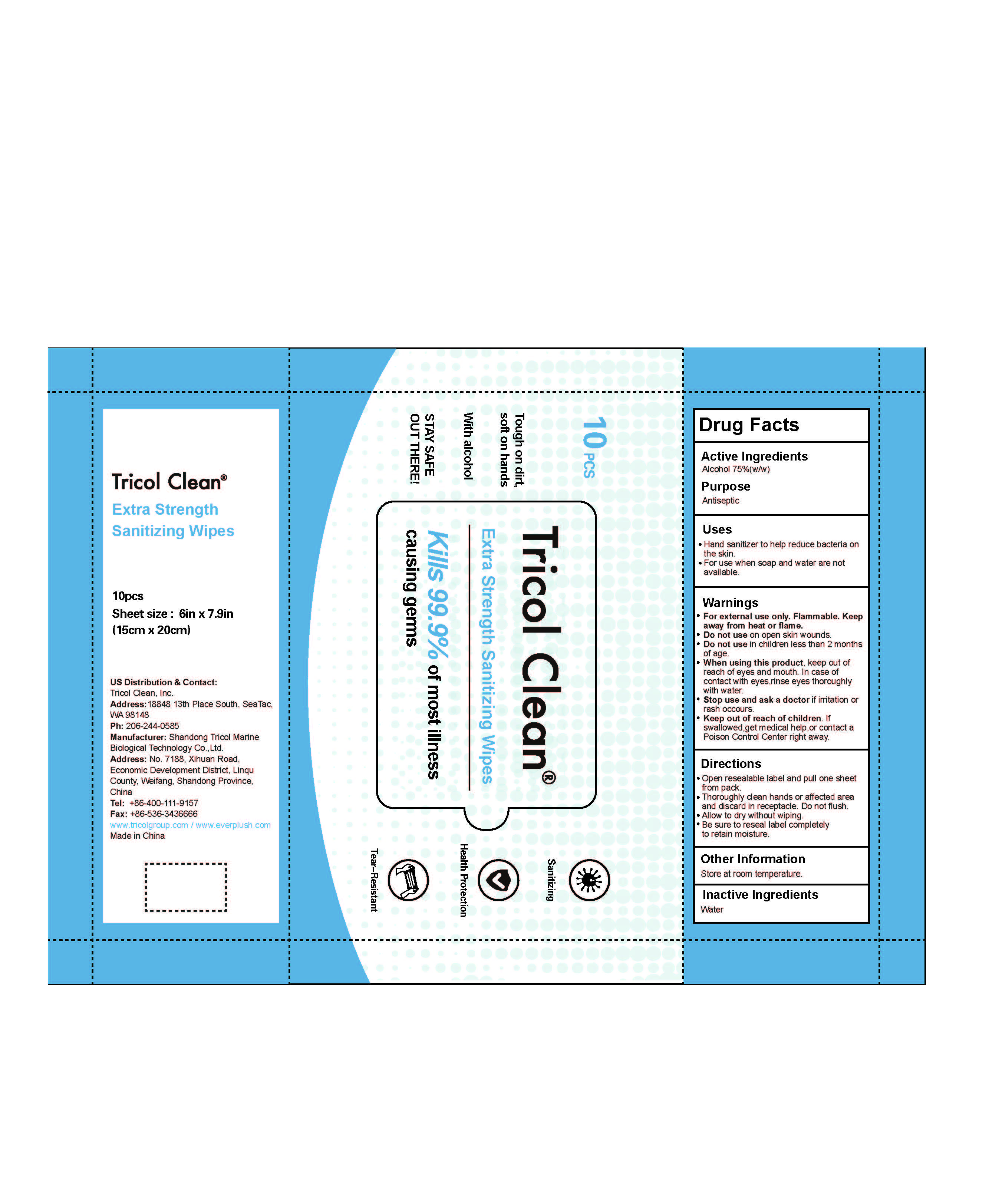 DRUG LABEL: Extra Strength Sanitizing Wipes
NDC: 54156-003 | Form: PATCH
Manufacturer: Shandong Tricol Marine Biological Technology Co.,Ltd
Category: otc | Type: HUMAN OTC DRUG LABEL
Date: 20210129

ACTIVE INGREDIENTS: ALCOHOL 75 g/100 g
INACTIVE INGREDIENTS: WATER

Active Ingredient(s)

Alcohol 75% w/w. Purpose: Antiseptic

Purpose

Antiseptic

Use

to help reduce bacteria on the skin. For use when soap and water are not available.

Warnings

For external use only. Flammable. Keep away from heat or flame

Do not use

- in children less than 2 months of age
- on open skin wounds

When using this product keep out of eyes, ears, and mouth. In case of contact with eyes, rinse eyes thoroughly with water.
Stop use and ask a doctor if irritation or rash occurs. These may be signs of a serious condition.
Keep out of reach of children. If swallowed, get medical help or contact a Poison Control Center right away.

Stop use and ask a doctor if irritation or rash occurs. These may be signs of a serious condition.

Keep out of reach of children. If swallowed, get medical help or contact a Poison Control Center right away.

Directions

- Open packet,remove and unfold pre-moistened tissue.
- Thoroughly clean hands or affected area and discard in receptacle.Do not flush.
- Allow to dry without wiping
- Be sure to reseal packet completely to retain moisture

Other information

Store at room temperature

Inactive ingredients

water